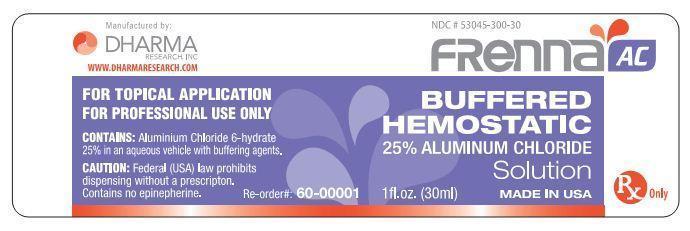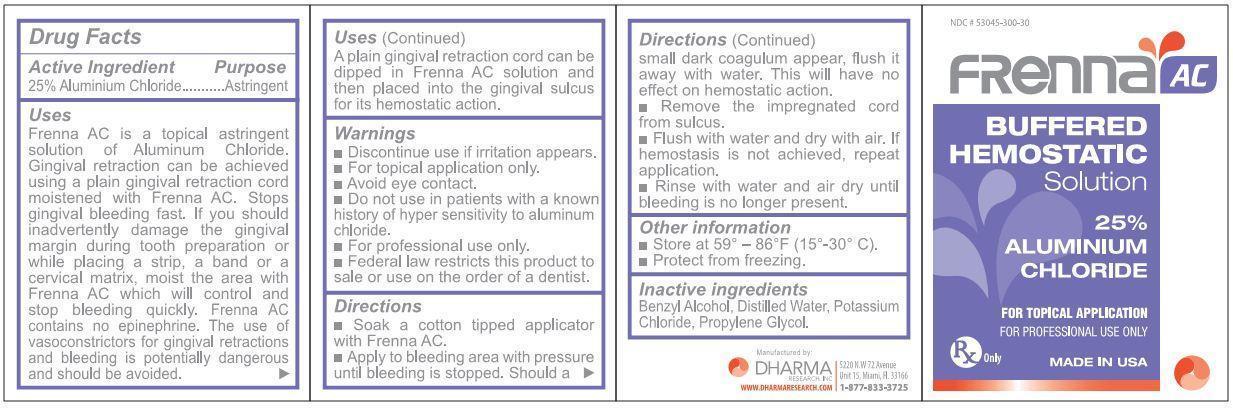 DRUG LABEL: Frenna AC
NDC: 53045-300 | Form: SOLUTION
Manufacturer: Dharma Research, inc.
Category: prescription | Type: HUMAN PRESCRIPTION DRUG LABEL
Date: 20201106

ACTIVE INGREDIENTS: ALUMINUM CHLORIDE 8.75 g/35 g
INACTIVE INGREDIENTS: WATER; POTASSIUM CHLORIDE; PROPYLENE GLYCOL; BENZYL ALCOHOL

STORAGE AND HANDLING

- Store at 59o - 86oF (15o - 30oC)
- Protect from freezing

INACTIVE INGREDIENT

Benzyl Alcohol, Distilled Water, Potassium Chloride, Propylene Glycol.

WARNINGS AND PRECAUTIONS

- Discontinue use if irritation appears.
- For topical application only.
- Avoid eye contact.
- Do not use in patients with a known history of hyper sensetivity to Aluminum Chloride.
- For professional use only.
- Federal law restricts this product to sale or use on the order of a dentist.

INSTRUCTIONS FOR USE

- Soak a cotton tipped applicator with Frenna AC.
- Apply to bleeding area with pressure until bleeding is stopped. Should a small dark coagulum appear, flush it away with water. This will have no effect on hemostatic action.
- Remove the impregnated cord from sulcus.
- Flush with water and dry with air. If hemostasis is not achieved, repeat application.
- Rinse with water and air dry until bleeding is no longer present.

INDICATIONS AND USAGE

Frenna AC is a topical astringent solution of Aluminum Chloride. Gingival retraction can be achieved using a plain gingival retraction cord moistened with Frenna AC. Stops gingival bleeding fast. If you should anadvertently damage the gingival margin during tooth preparation or while placing a strip, a band, or a cervical matrix, moisten the area with Frenna AC which will control and stop bleeding quickly. Frenna AC contains no epinephrine. The use of casoconstrictors for gingival retractions and bleeding is potentially dangerous and should be avoided.

A plain gingival retraction cord can be dipped in Frenna AC solution and then placed into the gingival sulcus for its hemostatic action.